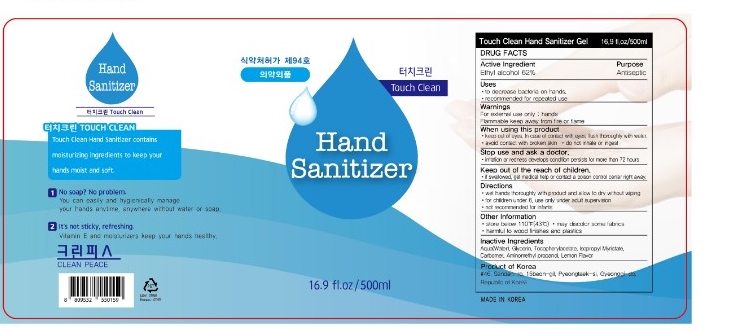 DRUG LABEL: Touch Clean
NDC: 77818-301 | Form: GEL
Manufacturer: Cleanpeace Co., Ltd
Category: otc | Type: HUMAN OTC DRUG LABEL
Date: 20221216

ACTIVE INGREDIENTS: ALCOHOL 62 mL/100 mL
INACTIVE INGREDIENTS: WATER 37.25 mL/100 mL; CARBOMER HOMOPOLYMER, UNSPECIFIED TYPE 0.3 mL/100 mL; AMINOMETHYLPROPANOL 0.1 mL/100 mL; GLYCERIN 0.1 mL/100 mL; ISOPROPYL MYRISTATE 0.1 mL/100 mL; .ALPHA.-TOCOPHEROL ACETATE 0.1 mL/100 mL; LEMON OIL 0.05 mL/100 mL

Active Ingredient

alchol 62%

PURPOSE

ANTIMICROBIAL

Inactive ingredient

Glycerin, Isopropyl Myristate, Tocopherol Acetate, Carbomer, Aminomethyl Propanol

lemon oil, water(aqua)

Direction

wet hands thoroughly with product and allow to dry without wiping

for children under 6, use only under adult supervision

not recommentded for infants

Do not use

do not inhale or ingest

avoid contact with briken skin

Warnings

for external use only: hands Flammable. keep away from heat or flame.

Keep out of reach of children.

If swallowed get medical help or contact a Poison Control center right away.

Stop use and ask a doctor.

irritation or redness develops condition persists for more than 72 hours

Use

to decrease bacteria on hands

recommended for repeated use

Other information

Store between 110'F(43'C)

may discolor some fabrics
harmful to wood finishes and plastics.

When using this product

Keep out of eyes, ears, and mouth in case of contact with eyes, rinse eyes thoroughly whit water.

avoid contact with broken skin

do not inhale or ingest

Pakage Label

Touch Clean Hand Sanitizer

500ML ndc:77818-301-01